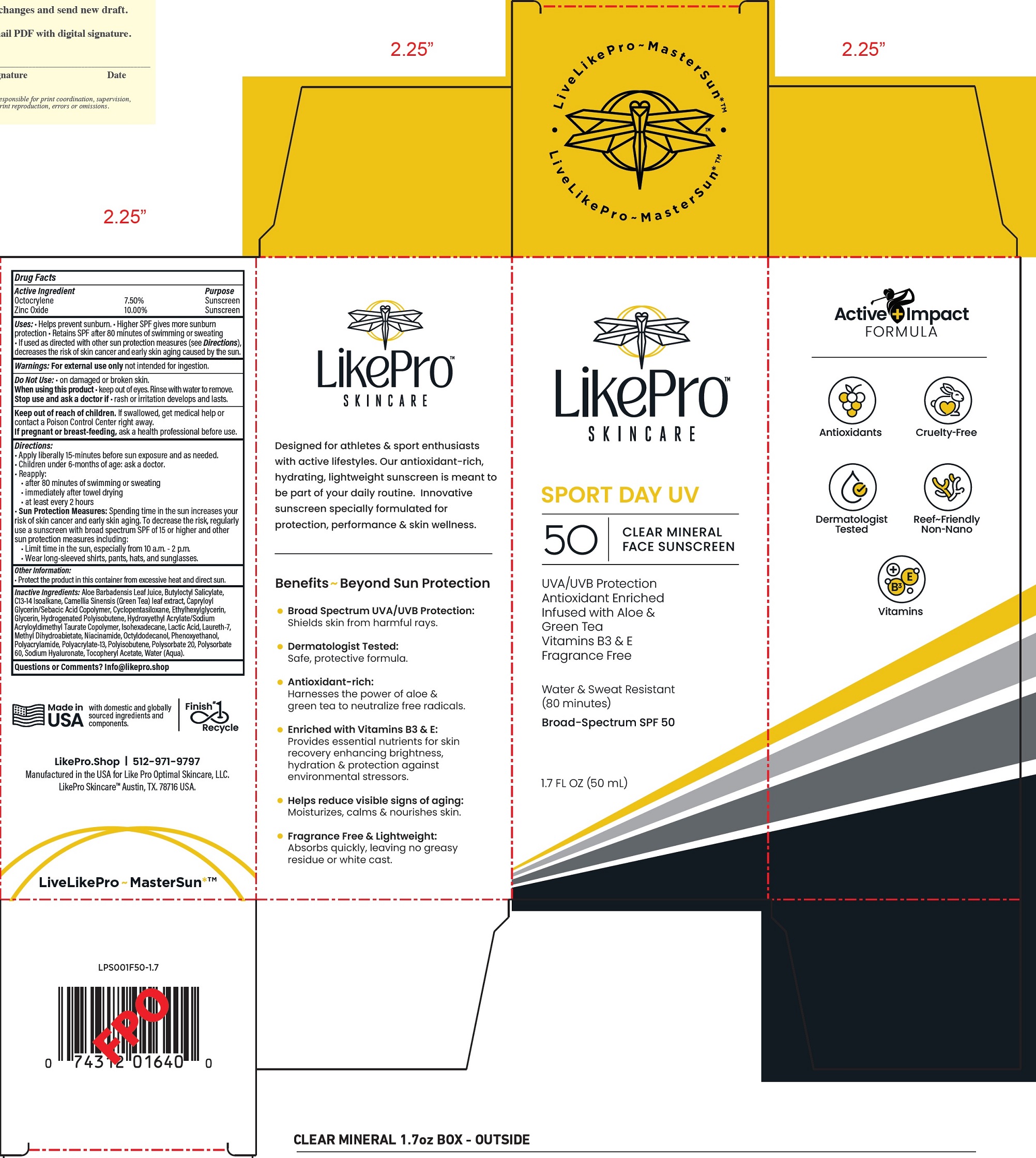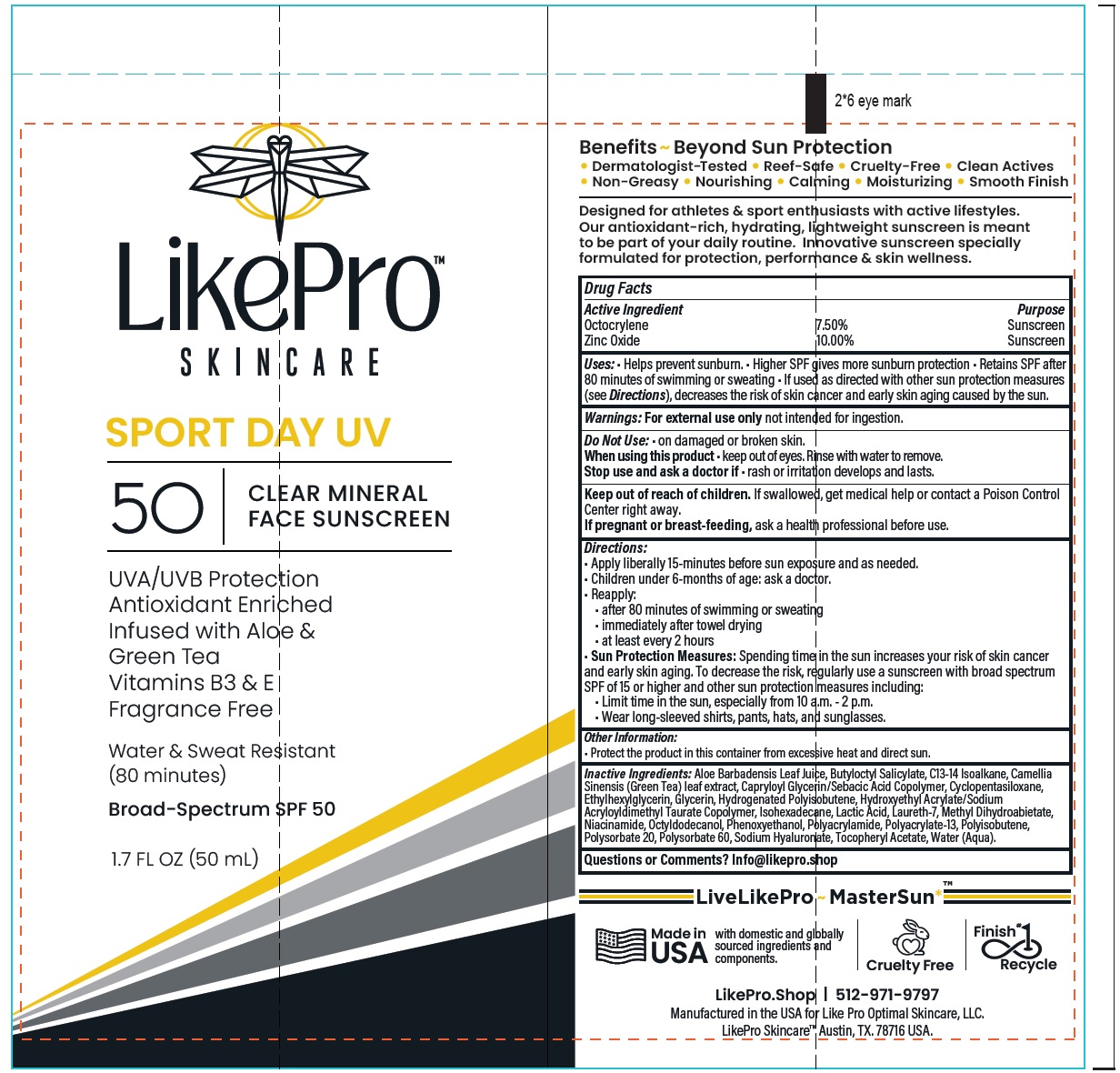 DRUG LABEL: LikePro Skincare Sport Day UV Face Sunscreen SPF 50
NDC: 85750-613 | Form: LOTION
Manufacturer: LIKE PRO OPTIMAL SKINCARE LLC
Category: otc | Type: HUMAN OTC DRUG LABEL
Date: 20250603

ACTIVE INGREDIENTS: OCTOCRYLENE 75 mg/1 mL; ZINC OXIDE 100 mg/1 mL
INACTIVE INGREDIENTS: ALOE VERA LEAF JUICE; ASCORBYL PALMITATE; BUTYLOCTYL SALICYLATE; C13-14 ISOPARAFFIN; GREEN TEA LEAF; CYCLOMETHICONE 5; ETHYLHEXYLGLYCERIN; GLYCERIN; ISOHEXADECANE; LACTIC ACID; LAURETH-7; METHYL DIHYDROABIETATE; NIACINAMIDE; OCTYLDODECANOL; PHENOXYETHANOL; POLYACRYLATE-13; POLYSORBATE 20; POLYSORBATE 60; SODIUM HYALURONATE; .ALPHA.-TOCOPHEROL ACETATE; WATER

LikePro Skincare Sport Day UV Face Sunscreen SPF 50

Active Ingredient

Octocrylene 7.50%
Zinc Oxide 17.50%

Purpose

Sunscreen

Uses:

- Helps prevent sunburn.
- Higher SPF gives more sunburn protection
- Retains SPF after 80 minutes of swimming or sweating
- If used as directed with other sun protection measures (see Directions), decreases the risk of skin cancer and early skin aging caused by the sun.

Warnings:

For external use only not intended for ingestion.

Do Not Use:

- on damaged or broken skin.

When using this product

- keep out of eyes. Rinse with water to remove.

Stop use and ask a doctor if

- rash or irritation develops and lasts.

Keep out of reach of children.

If swallowed, get medical help or contact a Poison Control Center right away.

If pregnant or breast-feeding,

ask a health professional before use.

Directions:

- Apply liberally 15-minutes before sun exposure and as needed.
- Children under 6-months of age: ask a doctor.
- Reapply:
- after 80 minutes of swimming or sweating
- immediately after towel drying
- at least every 2 hours
- Sun Protection Measures:Spending time in the sun increases your risk of skin cancer and early skin aging. To decrease the risk, regularly use a sunscreen with broad spectrum SPF of 15 or higher and other sun protection measures including:
- Limit time in the sun, especially from 10 a.m. - 2 p.m.
- Wear long-sleeved shirts, pants, hats, and sunglasses.

Other Information:

- Protect the product in this container from excessive heat and direct sun.

Inactive Ingredients:

Aloe Barbadensis Leaf Juice, Butyloctyl Salicylate, C13-14 Isoalkane, Camellia Sinensis (Green Tea) leaf extract, Capryloyl Glycerin/Sebacic Acid Copolymer, Cyclopentasiloxane, Ethylhexylglycerin, Glycerin, Hydrogenated Polyisobutene, Hydroxyethyl Acrylate/Sodium Acryloyldimethyl Taurate Copolymer, Isohexadecane, Lactic Acid, Laureth-7, Methyl Dihydroabietate, Niacinamide, Octyldodecanol, Phenoxyethanol, Polyacrylamide, Polyacrylate-13, Polyisobutene, Polysorbate 20, Polysorbate 60, Sodium Hyaluronate, Tocopheryl Acetate, Water (Aqua).

Questions or Comments?

Info@likepro.shop